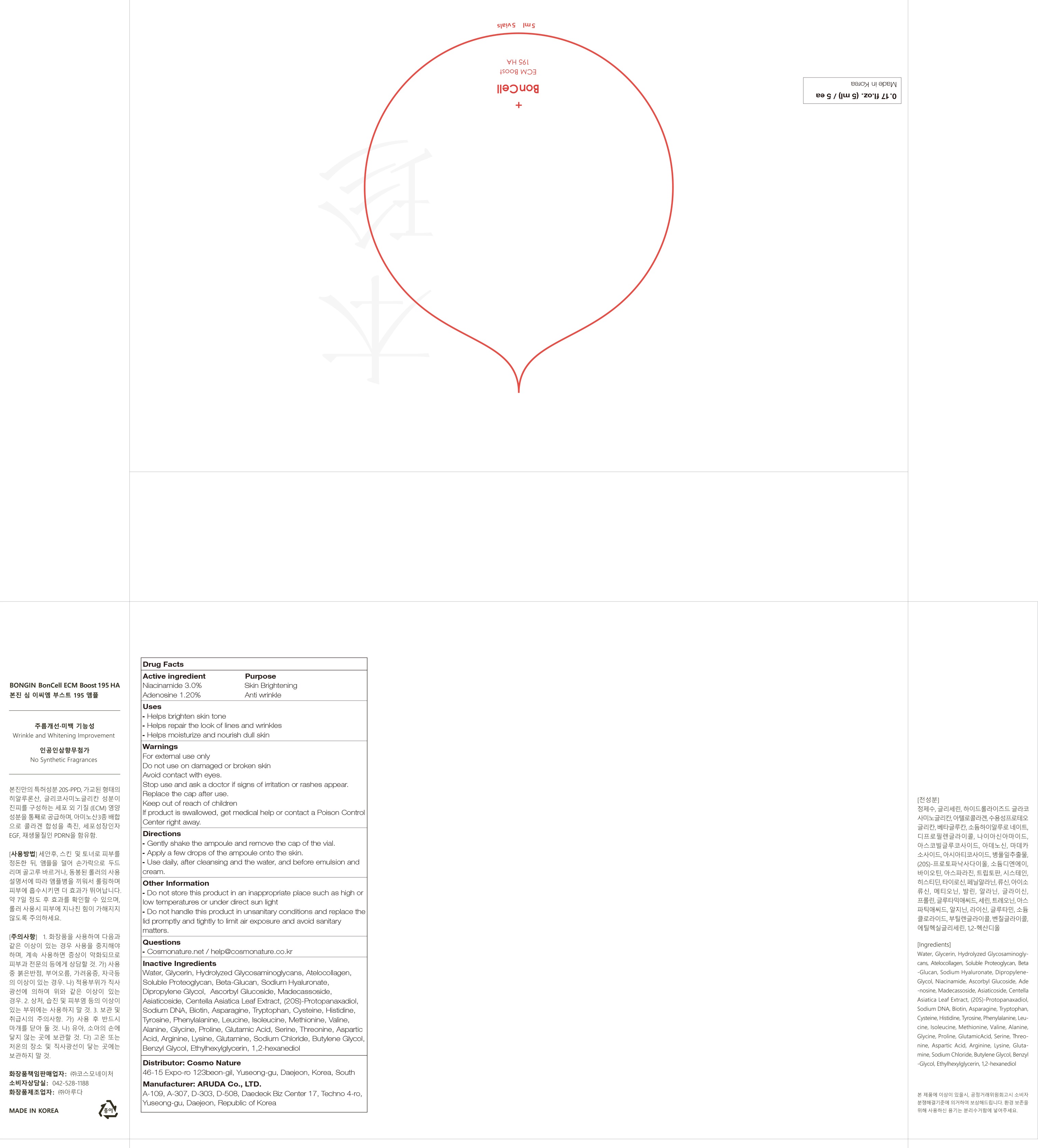 DRUG LABEL: BonGin BonCell ECM Boost 195 HA
NDC: 82492-050 | Form: LIQUID
Manufacturer: Cosmo Nature
Category: otc | Type: HUMAN OTC DRUG LABEL
Date: 20220218

ACTIVE INGREDIENTS: Niacinamide 3.0 g/100 mL; Adenosine 1.20 g/100 mL
INACTIVE INGREDIENTS: Water; Glycerin

ACTIVE INGREDIENTS

Niacinamide 3.0%
Adenosine 1.20%

INACTIVE INGREDIENTS

Water, Glycerin, Hydrolyzed Glycosaminoglycans, Atelocollagen, Soluble Proteoglycan, Beta-Glucan, Sodium Hyaluronate, Dipropylene Glycol, Ascorbyl Glucoside, Madecassoside, Asiaticoside, Centella Asiatica Leaf Extract, (20S)-Protopanaxadiol, Sodium DNA, Biotin, Asparagine, Tryptophan, Cysteine, Histidine, Tyrosine, Phenylalanine, Leucine, Isoleucine, Methionine, Valine, Alanine, Glycine, Proline, Glutamic Acid, Serine, Threonine, Aspartic Acid, Arginine, Lysine, Glutamine, Sodium Chloride, Butylene Glycol, Benzyl Glycol, Ethylhexylglycerin, 1,2-hexanediol

PURPOSE

Skin Brightening
Anti wrinkle

WARNINGS

For external use only
Do not use on damaged or broken skin
Avoid contact with eyes.
Stop use and ask a doctor if signs of irritation or rashes appear.
Replace the cap after use.
Keep out of reach of children
If product is swallowed, get medical help or contact a Poison Control Center right away.

KEEP OUT OF REACH OF CHILDREN

Uses

■ Helps brighten skin tone
■ Helps repair the look of lines and wrinkles
■ Helps moisturize and nourish dull skin

Directions

■ Gently shake the ampoule and remove the cap of the vial.
■ Apply a few drops of the ampoule onto the skin.
■ Use daily, after cleansing and the water, and before emulsion and cream.

Other Information

■ Do not store this product in an inappropriate place, such as in high or low temperatures or under direct sunlight.
■ Do not handle this product in unsanitary conditions and replace the lid promptly and tightly to limit air exposure and avoid sanitary matters.

Questions

■ Cosmonature.net / help@cosmonature.co.kr